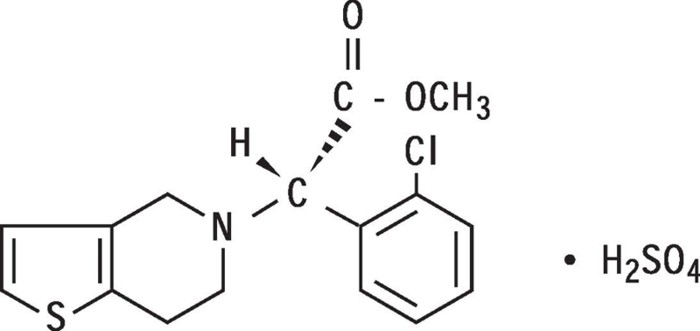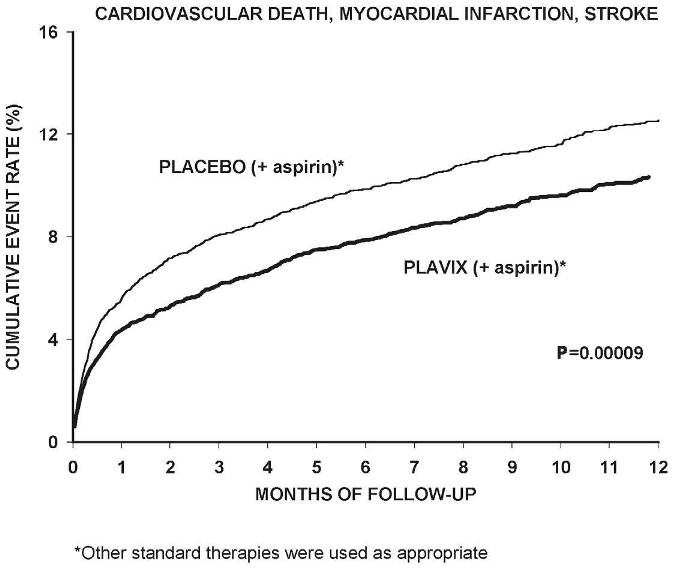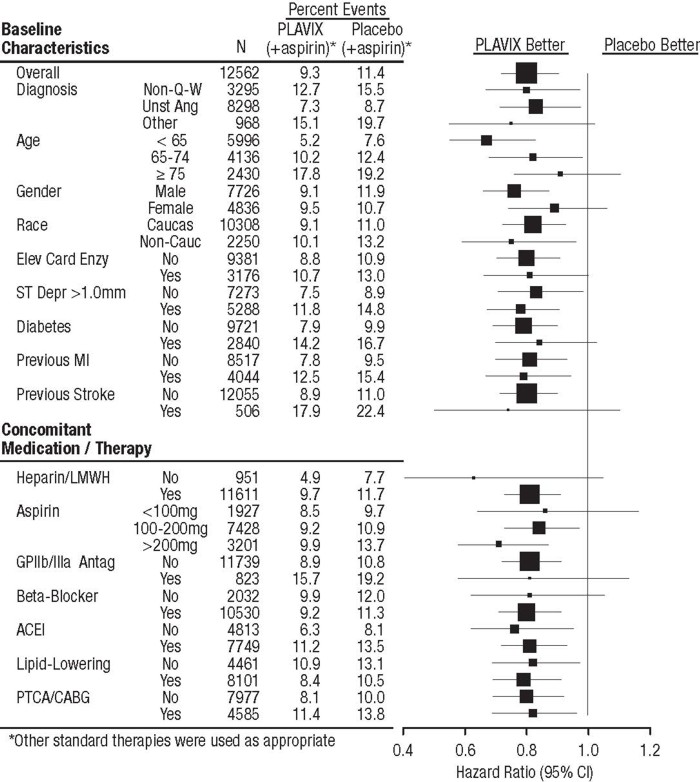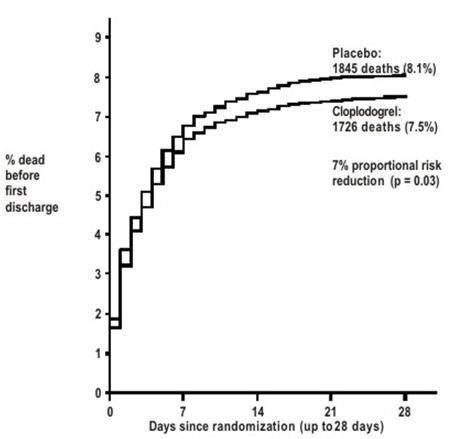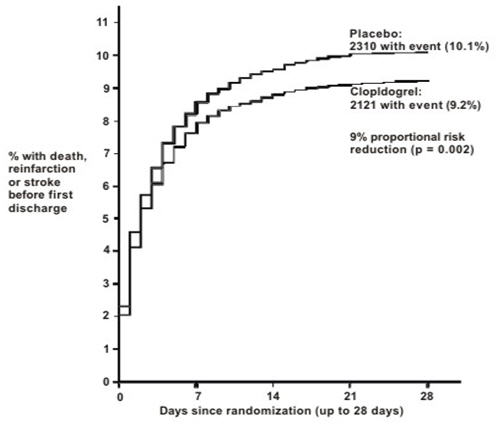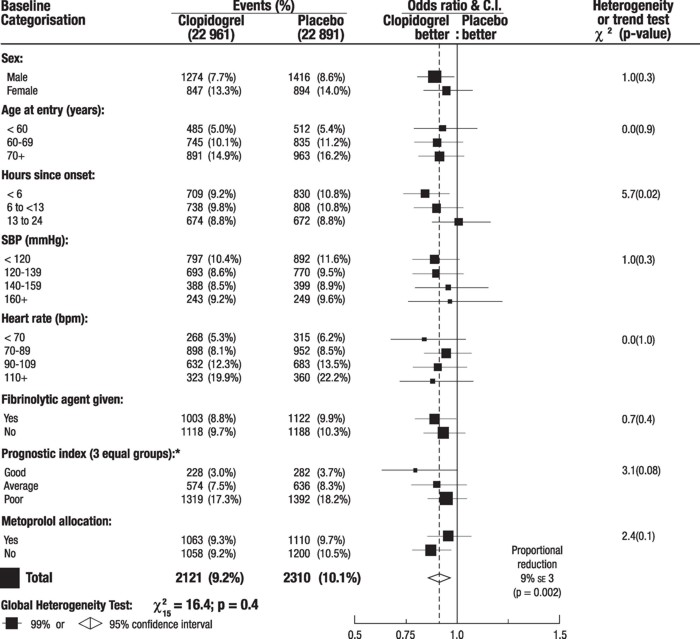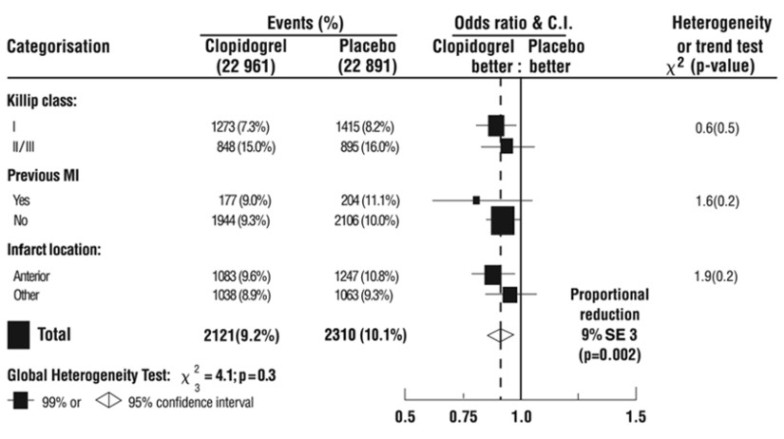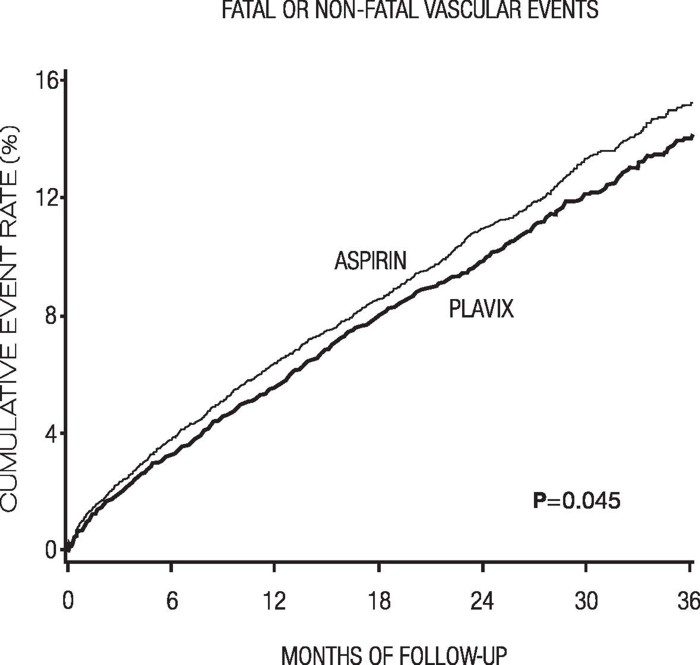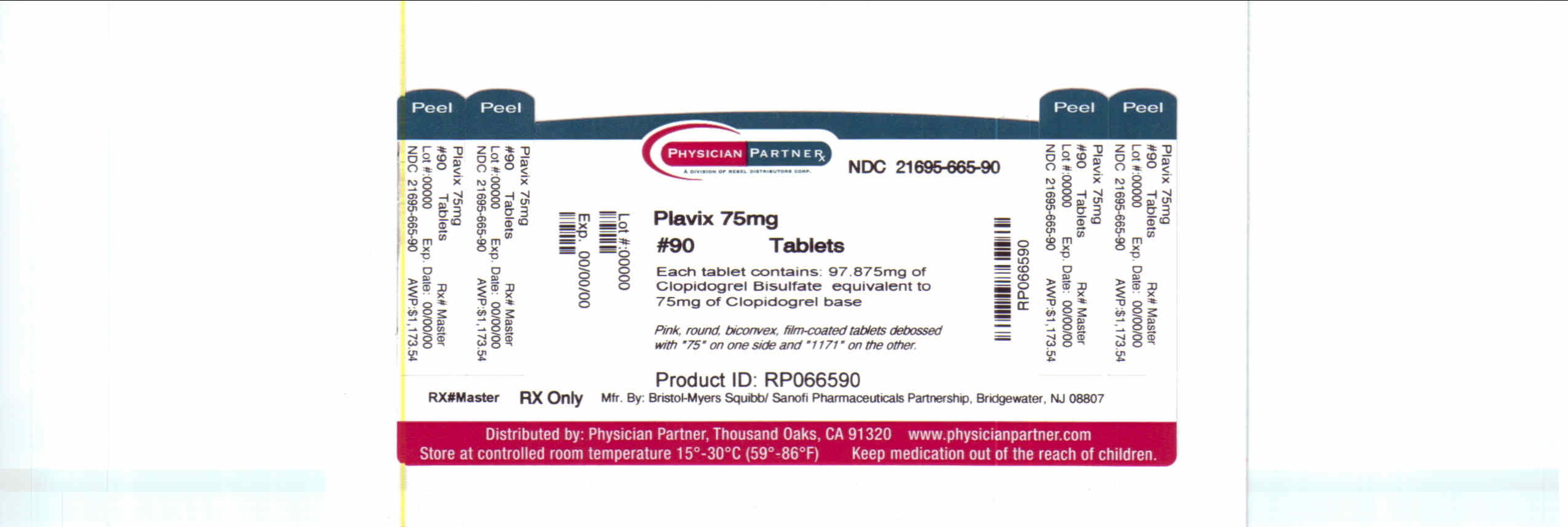 DRUG LABEL: Plavix
NDC: 21695-665 | Form: TABLET, FILM COATED
Manufacturer: Rebel Distributors Corp
Category: prescription | Type: HUMAN PRESCRIPTION DRUG LABEL
Date: 20101228

ACTIVE INGREDIENTS: clopidogrel bisulfate 75 mg/1 1
INACTIVE INGREDIENTS: castor oil; hydroxypropyl cellulose; mannitol; cellulose, microcrystalline; polyethylene glycol 6000; ferric oxide red; lactose monohydrate; titanium dioxide; triacetin; carnauba wax

HIGHLIGHTS OF PRESCRIBING INFORMATION

These highlights do not include all the information needed to use
PLAVIX safely and effectively. See full prescribing information for
PLAVIX.
PLAVIX (clopidogrel bisulfate) tablets
Initial U.S. Approval: 1997

RECENT MAJOR CHANGES

Boxed Warning | 03/2010
Dosage and Administration (2.3) | 03/2010
Warnings and Precautions (5.1, 5.2, 5.3) | 03/2010

WARNING: DIMINISHED EFFECTIVENESS IN POOR METABOLIZERS

See full prescribing information for complete boxed warning.

- Effectiveness of Plavix depends on activation to an active metabolite by the cytochrome P450 (CYP) system, principally CYP2C19. (5.1)
- Poor metabolizers treated with Plavix at recommended doses exhibit higher cardiovascular event rates following acute coronary syndrome (ACS) or percutaneous coronary intervention (PCI) than patients with normal CYP2C19 function. (12.5)
- Tests are available to identify a patient's CYP2C19 genotype and can be used as an aid in determining therapeutic strategy. (12.5)
- Consider alternative treatment or treatment strategies in patients identified as CYP2C19 poor metabolizers. (2.3, 5.1)

1 INDICATIONS AND USAGE

Plavix is a P2Y12 platelet inhibitor indicated for:

- Acute coronary syndrome
- Recent myocardial infarction (MI), recent stroke, or established peripheral arterial disease. Plavix has been shown to reduce the combined endpoint of new ischemic stroke (fatal or not), new MI (fatal or not), and other vascular death. (1.2)

2 DOSAGE AND ADMINISTRATION

- Acute coronary syndrome (2.1)
- Recent MI, recent stroke, or established peripheral arterial disease: 75 mg once daily (2.2)

3 DOSAGE FORMS AND STRENGTHS

Tablets: 75 mg, 300 mg (3)

4 CONTRAINDICATIONS

- Active pathological bleeding, such as peptic ulcer or intracranial hemorrhage (4.1)
- Hypersensitivity to clopidogrel or any component of the product (4.2)

5 WARNINGS AND PRECAUTIONS

- Reduced effectiveness in impaired CYP2C19 function: Avoid concomitant use with drugs that inhibit CYP2C19 (e.g., omeprazole). (5.1)
- Bleeding: Plavix increases risk of bleeding. Discontinue 5 days prior to elective surgery. (5.2)
- Discontinuation of Plavix: Premature discontinuation increases risk of cardiovascular events. (5.3)
- Recent transient ischemic attack or stroke: Combination use of Plavix and aspirin in these patients was not shown to be more effective than Plavix alone, but was shown to increase major bleeding. (5.4)
- Thrombotic thrombocytopenic purpura (TTP): TTP has been reported with Plavix, including fatal cases. (5.5)

6 ADVERSE REACTIONS

Bleeding, including life-threatening and fatal bleeding, is the most commonly reported adverse reaction. (6.1)

To report SUSPECTED ADVERSE REACTIONS, contact Bristol-Myers Squibb/Sanofi Pharmaceuticals Partnership at 1-800-633-1610 or FDA at 1-800-FDA-1088 or www.fda.gov/medwatch.

7 DRUG INTERACTIONS

- CYP2C19 inhibitors (e.g., omeprazole): Avoid concomitant use. (7.1)
- Nonsteroidal anti-inflammatory drugs (NSAIDs): Combination use increases risk of gastrointestinal bleeding. (7.2)
- Warfarin: Combination use increases risk of bleeding. (7.3)

8 USE IN SPECIFIC POPULATIONS

Nursing mothers: Discontinue drug or nursing, taking into consideration importance of drug to mother. (8.3)

FULL PRESCRIBING INFORMATION

WARNING: DIMINISHED EFFECTIVENESS IN POOR METABOLIZERS

The effectiveness of Plavix is dependent on its activation to an active metabolite by the cytochrome P450 (CYP) system, principally CYP2C19 [see Warnings and Precautions (5.1)]. Plavix at recommended doses forms less of that metabolite and has a smaller effect on platelet function in patients who are CYP2C19 poor metabolizers. Poor metabolizers with acute coronary syndrome or undergoing percutaneous coronary intervention treated with Plavix at recommended doses exhibit higher cardiovascular event rates than do patients with normal CYP2C19 function. Tests are available to identify a patient's CYP2C19 genotype; these tests can be used as an aid in determining therapeutic strategy [see Clinical Pharmacology (12.5)]. Consider alternative treatment or treatment strategies in patients identified as CYP2C19 poor metabolizers [see Dosage and Administration (2.3)].

1 INDICATIONS AND USAGE

1.1 Acute Coronary Syndrome (ACS)

- For patients with non-ST-segment elevation ACS [unstable angina (UA)/non-ST-elevation myocardial infarction (NSTEMI)], including patients who are to be managed medically and those who are to be managed with coronary revascularization, Plavix has been shown to decrease the rate of a combined endpoint of cardiovascular death, myocardial infarction (MI), or stroke as well as the rate of a combined endpoint of cardiovascular death, MI, stroke, or refractory ischemia.
- For patients with ST-elevation myocardial infarction (STEMI), Plavix has been shown to reduce the rate of death from any cause and the rate of a combined endpoint of death, re-infarction, or stroke. The benefit for patients who undergo primary percutaneous coronary intervention is unknown.

The optimal duration of Plavix therapy in ACS is unknown.

1.2 Recent MI, Recent Stroke, or Established Peripheral Arterial Disease

For patients with a history of recent myocardial infarction (MI), recent stroke, or established peripheral arterial disease, Plavix has been shown to reduce the rate of a combined endpoint of new ischemic stroke (fatal or not), new MI (fatal or not), and other vascular death.

2 DOSAGE AND ADMINISTRATION

2.1 Acute Coronary Syndrome

Plavix can be administered with or without food [see Clinical Pharmacology (12.3)]

- For patients with non-ST-elevation ACS (UA/NSTEMI), initiate Plavix with a single 300 mg oral loading dose and then continue at 75 mg once daily. Initiate aspirin (75–325 mg once daily) and continue in combination with Plavix [see Clinical Studies (14.1)].
- For patients with STEMI, the recommended dose of Plavix is 75 mg once daily orally, administered in combination with aspirin (75–325 mg once daily), with or without thrombolytics. Plavix may be initiated with or without a loading dose [see Clinical Studies (14.1)].

2.2 Recent MI, Recent Stroke, or Established Peripheral Arterial Disease

The recommended daily dose of Plavix is 75 mg once daily orally, with or without food [see Clinical Pharmacology (12.3)].

2.3 CYP2C19 Poor Metabolizers

CYP2C19 poor metabolizer status is associated with diminished antiplatelet response to clopidogrel. Although a higher dose regimen (600 mg loading dose followed by 150 mg once daily) in poor metabolizers increases antiplatelet response [see Clinical Pharmacology (12.5)], an appropriate dose regimen for this patient population has not been established in clinical outcome trials.

3 DOSAGE FORMS AND STRENGTHS

- 75 mg tablets: Pink, round, biconvex, film-coated tablets debossed with "75" on one side and "1171" on the other
- 300 mg tablets: Pink, oblong, film-coated tablets debossed with "300" on one side and "1332" on the other

4 CONTRAINDICATIONS

4.1 Active Bleeding

Plavix is contraindicated in patients with active pathological bleeding such as peptic ulcer or intracranial hemorrhage.

4.2 Hypersensitivity

Plavix is contraindicated in patients with hypersensitivity (e.g., anaphylaxis) to clopidogrel or any component of the product [see Adverse Reactions (6.2)].

5 WARNINGS AND PRECAUTIONS

5.1 Diminished Antiplatelet Activity Due to Impaired CYP2C19 Function

Clopidogrel is a prodrug. Inhibition of platelet aggregation by clopidogrel is entirely due to an active metabolite. The metabolism of clopidogrel to its active metabolite can be impaired by genetic variations in CYP2C19 [see Boxed Warning] and by concomitant medications that interfere with CYP2C19. Avoid concomitant use of Plavix and drugs that inhibit CYP2C19 activity. Co-administration of Plavix with omeprazole, a proton pump inhibitor that is an inhibitor of CYP2C19, reduces the pharmacological activity of Plavix if given concomitantly or if given 12 hours apart [see Drug Interactions (7.1)].

5.2 General Risk of Bleeding

Thienopyridines, including Plavix, increase the risk of bleeding. If a patient is to undergo surgery and an antiplatelet effect is not desired, discontinue Plavix 5 days prior to surgery. In patients who stopped therapy more than five days prior to CABG the rates of major bleeding were similar (event rate 4.4% Plavix + aspirin; 5.3% placebo + aspirin). In patients who remained on therapy within five days of CABG, the major bleeding rate was 9.6% for Plavix + aspirin, and 6.3% for placebo + aspirin.

Thienopyridines inhibit platelet aggregation for the lifetime of the platelet (7–10 days), so withholding a dose will not be useful in managing a bleeding event or the risk of bleeding associated with an invasive procedure. Because the half-life of clopidogrel's active metabolite is short, it may be possible to restore hemostasis by administering exogenous platelets; however, platelet transfusions within 4 hours of the loading dose or 2 hours of the maintenance dose may be less effective.

5.3 Discontinuation of Plavix

Avoid lapses in therapy, and if Plavix must be temporarily discontinued, restart as soon as possible. Premature discontinuation of Plavix may increase the risk of cardiovascular events.

5.4 Patients with Recent Transient Ischemic Attack (TIA) or Stroke

In patients with recent TIA or stroke who are at high risk for recurrent ischemic events, the combination of aspirin and Plavix has not been shown to be more effective than Plavix alone, but the combination has been shown to increase major bleeding.

5.5 Thrombotic Thrombocytopenic Purpura (TTP)

TTP, sometimes fatal, has been reported following use of Plavix, sometimes after a short exposure (<2 weeks). TTP is a serious condition that requires urgent treatment including plasmapheresis (plasma exchange). It is characterized by thrombocytopenia, microangiopathic hemolytic anemia (schistocytes [fragmented RBCs] seen on peripheral smear), neurological findings, renal dysfunction, and fever [see Adverse Reactions (6.2)].

6 ADVERSE REACTIONS

The following serious adverse reactions are discussed below and elsewhere in the labeling:

- Bleeding [see Warnings and Precautions (5.2)]
- Thrombotic thrombocytopenic purpura [see Warnings and Precautions (5.5)]

6.1 Clinical Studies Experience

Because clinical trials are conducted under widely varying conditions and durations of follow up, adverse reaction rates observed in the clinical trials of a drug cannot be directly compared to rates in the clinical trials of another drug and may not reflect the rates observed in practice.

Plavix has been evaluated for safety in more than 54,000 patients, including over 21,000 patients treated for 1 year or more. The clinically important adverse reactions observed in trials comparing Plavix plus aspirin to placebo plus aspirin and trials comparing Plavix alone to aspirin alone are discussed below.

Bleeding

CURE

In CURE, Plavix use with aspirin was associated with an increase in major bleeding (primarily gastrointestinal and at puncture sites) compared to placebo with aspirin (see Table 1). The incidence of intracranial hemorrhage (0.1%) and fatal bleeding (0.2%) were the same in both groups. Other bleeding events that were reported more frequently in the clopidogrel group were epistaxis, hematuria, and bruise.

The overall incidence of bleeding is described in Table 1.

Table 1: CURE Incidence of Bleeding Complications (% patients)
Event | Plavix (+ aspirin) [Other standard therapies were used as appropriate.] | Placebo (+ aspirin) | p-value
 | (n=6259) | (n=6303)
Major bleeding [Life-threatening and other major bleeding.] | 3.7 [Major bleeding event rate for Plavix + aspirin was dose-dependent on aspirin: <100 mg = 2.6%; 100–200 mg = 3.5%; >200 mg = 4.9% Major bleeding event rates for Plavix + aspirin by age were: <65 years = 2.5%, ≥65 to <75 years = 4.1%, ≥75 years = 5.9%] | 2.7 [Major bleeding event rate for placebo + aspirin was dose-dependent on aspirin: <100 mg = 2.0%; 100–200 mg = 2.3%; >200 mg = 4.0% Major bleeding event rates for placebo + aspirin by age were: <65 years = 2.1%, ≥65 to <75 years = 3.1%, ≥75 years = 3.6%] | 0.001
Life-threatening bleeding | 2.2 | 1.8 | 0.13
Fatal | 0.2 | 0.2
5 g/dL hemoglobin drop | 0.9 | 0.9
Requiring surgical intervention | 0.7 | 0.7
Hemorrhagic strokes | 0.1 | 0.1
Requiring inotropes | 0.5 | 0.5
Requiring transfusion (≥4 units) | 1.2 | 1.0
Other major bleeding | 1.6 | 1.0 | 0.005
Significantly disabling | 0.4 | 0.3
Intraocular bleeding with significant loss of vision | 0.05 | 0.03
Requiring 2–3 units of blood | 1.3 | 0.9
Minor bleeding [Led to interruption of study medication.] | 5.1 | 2.4 | < 0.001

Ninety-two percent (92%) of the patients in the CURE study received heparin or low molecular weight heparin (LMWH), and the rate of bleeding in these patients was similar to the overall results.

COMMIT

In COMMIT, similar rates of major bleeding were observed in the Plavix and placebo groups, both of which also received aspirin (see Table 2).

Table 2: Incidence of Bleeding Events in COMMIT (% patients)
Type of bleeding | Plavix (+ aspirin) (n=22961) | Placebo (+ aspirin) (n=22891) | p-value
Major [Major bleeds were cerebral bleeds or non-cerebral bleeds thought to have caused death or that required transfusion.] noncerebral or cerebral bleeding [The relative rate of major noncerebral or cerebral bleeding was independent of age. Event rates for Plavix + aspirin by age were: <60 years = 0.3%, ≥60 to <70 years = 0.7%, ≥70 years = 0.8%. Event rates for placebo + aspirin by age were: <60 years = 0.4%, ≥60 to <70 years = 0.6%, ≥70 years = 0.7%.] | 0.6 | 0.5 | 0.59
Major noncerebral | 0.4 | 0.3 | 0.48
Fatal | 0.2 | 0.2 | 0.90
Hemorrhagic stroke | 0.2 | 0.2 | 0.91
Fatal | 0.2 | 0.2 | 0.81
Other noncerebral bleeding (non-major) | 3.6 | 3.1 | 0.005
Any noncerebral bleeding | 3.9 | 3.4 | 0.004

CAPRIE (Plavix vs. Aspirin)

In CAPRIE, gastrointestinal hemorrhage occurred at a rate of 2.0% in those taking Plavix vs. 2.7% in those taking aspirin; bleeding requiring hospitalization occurred in 0.7% and 1.1%, respectively. The incidence of intracranial hemorrhage was 0.4% for Plavix compared to 0.5% for aspirin.

Other bleeding events that were reported more frequently in the Plavix group were epistaxis and hematoma.

Other Adverse Events

In CURE and CHARISMA, which compared Plavix plus aspirin to aspirin alone, there was no difference in the rate of adverse events (other than bleeding) between Plavix and placebo.

In CAPRIE, which compared Plavix to aspirin, pruritus was more frequently reported in those taking Plavix. No other difference in the rate of adverse events (other than bleeding) was reported.

6.2 Postmarketing Experience

The following adverse reactions have been identified during post-approval use of Plavix. Because these reactions are reported voluntarily from a population of an unknown size, it is not always possible to reliably estimate their frequency or establish a causal relationship to drug exposure.

- Blood and lymphatic system disorders: Agranulocytosis, aplastic anemia/pancytopenia, thrombotic thrombocytopenic purpura (TTP)
- Gastrointestinal disorders: Gastrointestinal and retroperitoneal hemorrhage with fatal outcome, colitis (including ulcerative or lymphocytic colitis), pancreatitis, stomatitis
- General disorders and administration site condition: Fever, hemorrhage of operative wound
- Hepato-biliary disorders: Acute liver failure, hepatitis (non-infectious), abnormal liver function test
- Immune system disorders: Hypersensitivity reactions, anaphylactoid reactions, serum sickness
- Musculoskeletal, connective tissue and bone disorders: Musculoskeletal bleeding, myalgia, arthralgia, arthritis
- Nervous system disorders: Taste disorders, fatal intracranial bleeding
- Eye disorders: Eye (conjunctival, ocular, retinal) bleeding
- Psychiatric disorders: Confusion, hallucinations
- Respiratory, thoracic and mediastinal disorders: Bronchospasm, interstitial pneumonitis, respiratory tract bleeding
- Renal and urinary disorders: Glomerulopathy, increased creatinine levels
- Skin and subcutaneous tissue disorders: Maculopapular or erythematous rash, urticaria, bullous dermatitis, eczema, toxic epidermal necrolysis, Stevens-Johnson syndrome, angioedema, erythema multiforme, skin bleeding, lichen planus
- Vascular disorders: Vasculitis, hypotension

7 DRUG INTERACTIONS

7.1 CYP2C19 Inhibitors

Clopidogrel is metabolized to its active metabolite in part by CYP2C19. Concomitant use of drugs that inhibit the activity of this enzyme results in reduced plasma concentrations of the active metabolite of clopidogrel and a reduction in platelet inhibition. Avoid concomitant use of drugs that inhibit CYP2C19, e.g., omeprazole [see Warnings and Precautions (5.1) and Clinical Pharmacology (12.5)].

Omeprazole

In a crossover clinical study, 72 healthy subjects were administered Plavix (300 mg loading dose followed by 75 mg per day) alone and with omeprazole (80 mg at the same time as Plavix) for 5 days. The exposure to the active metabolite of clopidogrel was decreased by 46% (Day 1) and 42% (Day 5) when Plavix and omeprazole were administered together. Mean inhibition of platelet aggregation was diminished by 47% (24 hours) and 30% (Day 5) when Plavix and omeprazole were administered together.

In another study, 72 healthy subjects were given the same doses of Plavix and omeprazole but the drugs were administered 12 hours apart; the results were similar, indicating that administering Plavix and omeprazole at different times does not prevent their interaction [see Warnings and Precautions (5.1)].

7.2 Nonsteroidal Anti-Inflammatory Drugs (NSAIDs)

Coadministration of Plavix and NSAIDs increases the risk of gastrointestinal bleeding.

7.3 Warfarin (CYP2C9 Substrates)

Although the administration of clopidogrel 75 mg per day did not modify the pharmacokinetics of S-warfarin (a CYP2C9 substrate) or INR in patients receiving long-term warfarin therapy, coadministration of Plavix with warfarin increases the risk of bleeding because of independent effects on hemostasis.

However, at high concentrations in vitro, clopidogrel inhibits CYP2C9.

8 USE IN SPECIFIC POPULATIONS

8.1 Pregnancy

Pregnancy Category B

Reproduction studies performed in rats and rabbits at doses up to 500 and 300 mg/kg/day, respectively (65 and 78 times the recommended daily human dose, respectively, on a mg/m^2 basis), revealed no evidence of impaired fertility or fetotoxicity due to clopidogrel. There are, however, no adequate and well-controlled studies in pregnant women. Because animal reproduction studies are not always predictive of a human response, Plavix should be used during pregnancy only if clearly needed.

8.3 Nursing Mothers

Studies in rats have shown that clopidogrel and/or its metabolites are excreted in the milk. It is not known whether this drug is excreted in human milk. Because many drugs are excreted in human milk and because of the potential for serious adverse reactions in nursing infants from clopidogrel, a decision should be made whether to discontinue nursing or to discontinue the drug, taking into account the importance of the drug to the mother.

8.4 Pediatric Use

Safety and effectiveness in the pediatric population have not been established.

8.5 Geriatric Use

Of the total number of subjects in the CAPRIE and CURE controlled clinical studies, approximately 50% of patients treated with Plavix were 65 years of age and older, and 15% were 75 years and older. In COMMIT, approximately 58% of the patients treated with Plavix were 60 years and older, 26% of whom were 70 years and older.

The observed risk of thrombotic events with clopidogrel plus aspirin versus placebo plus aspirin by age category is provided in Figures 2 and 5 for the CURE and COMMIT trials, respectively [see Clinical Studies (14.1)]. The observed risk of bleeding events with clopidogrel plus aspirin versus placebo plus aspirin by age category is provided in Tables 1 and 2 for the CURE and COMMIT trials, respectively [see Adverse Reactions (6.1)]. No dosage adjustment is necessary in elderly patients.

8.6 Renal Impairment

Experience is limited in patients with severe and moderate renal impairment [see Clinical Pharmacology (12.2)].

8.7 Hepatic Impairment

No dosage adjustment is necessary in patients with hepatic impairment [see Clinical Pharmacology (12.2)].

10 OVERDOSAGE

Platelet inhibition by Plavix is irreversible and will last for the life of the platelet. Overdose following clopidogrel administration may result in bleeding complications. A single oral dose of clopidogrel at 1500 or 2000 mg/kg was lethal to mice and to rats and at 3000 mg/kg to baboons. Symptoms of acute toxicity were vomiting, prostration, difficult breathing, and gastrointestinal hemorrhage in animals.

Based on biological plausibility, platelet transfusion may restore clotting ability.

11 DESCRIPTION

Plavix (clopidogrel bisulfate) is a thienopyridine class inhibitor of P2Y12 ADP platelet receptors. Chemically it is methyl (+)-(S)-α-(2-chlorophenyl)-6,7-dihydrothieno[3,2-c]pyridine-5(4H)-acetate sulfate (1:1). The empirical formula of clopidogrel bisulfate is C16H16ClNO2S•H2SO4 and its molecular weight is 419.9.

The structural formula is as follows:

Clopidogrel bisulfate is a white to off-white powder. It is practically insoluble in water at neutral pH but freely soluble at pH 1. It also dissolves freely in methanol, dissolves sparingly in methylene chloride, and is practically insoluble in ethyl ether. It has a specific optical rotation of about +56°.

Plavix for oral administration is provided as either pink, round, biconvex, debossed, film-coated tablets containing 97.875 mg of clopidogrel bisulfate which is the molar equivalent of 75 mg of clopidogrel base or pink, oblong, debossed film-coated tablets containing 391.5 mg of clopidogrel bisulfate which is the molar equivalent of 300 mg of clopidogrel base.

Each tablet contains hydrogenated castor oil, hydroxypropylcellulose, mannitol, microcrystalline cellulose and polyethylene glycol 6000 as inactive ingredients. The pink film coating contains ferric oxide, hypromellose 2910, lactose monohydrate, titanium dioxide and triacetin. The tablets are polished with Carnauba wax.

12 CLINICAL PHARMACOLOGY

12.1 Mechanism of Action

Clopidogrel is an inhibitor of platelet activation and aggregation through the irreversible binding of its active metabolite to the P2Y12 class of ADP receptors on platelets.

12.2 Pharmacodynamics

Clopidogrel must be metabolized by CYP450 enzymes to produce the active metabolite that inhibits platelet aggregation. The active metabolite of clopidogrel selectively inhibits the binding of adenosine diphosphate (ADP) to its platelet P2Y12 receptor and the subsequent ADP-mediated activation of the glycoprotein GPIIb/IIIa complex, thereby inhibiting platelet aggregation. This action is irreversible. Consequently, platelets exposed to clopidogrel's active metabolite are affected for the remainder of their lifespan (about 7 to 10 days). Platelet aggregation induced by agonists other than ADP is also inhibited by blocking the amplification of platelet activation by released ADP.

Dose-dependent inhibition of platelet aggregation can be seen 2 hours after single oral doses of Plavix. Repeated doses of 75 mg Plavix per day inhibit ADP-induced platelet aggregation on the first day, and inhibition reaches steady state between Day 3 and Day 7. At steady state, the average inhibition level observed with a dose of 75 mg Plavix per day was between 40% and 60%. Platelet aggregation and bleeding time gradually return to baseline values after treatment is discontinued, generally in about 5 days.

Geriatric Patients

Elderly (≥75 years) and young healthy subjects had similar effects on platelet aggregation.

Renally-Impaired Patients

After repeated doses of 75 mg Plavix per day, patients with severe renal impairment (creatinine clearance from 5 to 15 mL/min) and moderate renal impairment (creatinine clearance from 30 to 60 mL/min) showed low (25%) inhibition of ADP-induced platelet aggregation.

Hepatically-Impaired Patients

After repeated doses of 75 mg Plavix per day for 10 days in patients with severe hepatic impairment, inhibition of ADP-induced platelet aggregation was similar to that observed in healthy subjects.

Gender

In a small study comparing men and women, less inhibition of ADP-induced platelet aggregation was observed in women.

12.3 Pharmacokinetics

Clopidogrel is a prodrug and is metabolized to a pharmacologically active metabolite and inactive metabolites.

Absorption

After single and repeated oral doses of 75 mg per day, clopidogrel is rapidly absorbed. Absorption is at least 50%, based on urinary excretion of clopidogrel metabolites.

Effect of Food

Plavix can be administered with or without food. In a study in healthy male subjects when Plavix 75 mg per day was given with a standard breakfast, mean inhibition of ADP-induced platelet aggregation was reduced by less than 9%. The active metabolite AUC0–24 was unchanged in the presence of food, while there was a 57% decrease in active metabolite Cmax. Similar results were observed when a Plavix 300 mg loading dose was administered with a high-fat breakfast.

Metabolism

Clopidogrel is extensively metabolized by two main metabolic pathways: one mediated by esterases and leading to hydrolysis into an inactive carboxylic acid derivative (85% of circulating metabolites) and one mediated by multiple cytochrome P450 enzymes. Cytochromes first oxidize clopidogrel to a 2-oxo-clopidogrel intermediate metabolite. Subsequent metabolism of the 2-oxo-clopidogrel intermediate metabolite results in formation of the active metabolite, a thiol derivative of clopidogrel. This metabolic pathway is mediated by CYP2C19, CYP3A, CYP2B6 and CYP1A2. The active thiol metabolite binds rapidly and irreversibly to platelet receptors, thus inhibiting platelet aggregation for the lifespan of the platelet.

The Cmax of the active metabolite is twice as high following a single 300 mg clopidogrel loading dose as it is after four days of 75 mg maintenance dose. Cmax occurs approximately 30 to 60 minutes after dosing. In the 75 to 300 mg dose range, the pharmacokinetics of the active metabolite deviates from dose proportionality: increasing the dose by a factor of four results in 2.0- and 2.7-fold increases in Cmax and AUC, respectively.

Elimination

Following an oral dose of ^14C-labeled clopidogrel in humans, approximately 50% of total radioactivity was excreted in urine and approximately 46% in feces over the 5 days post-dosing. After a single, oral dose of 75 mg, clopidogrel has a half-life of approximately 6 hours. The half-life of the active metabolite is about 30 minutes.

12.5 Pharmacogenomics

CYP2C19 is involved in the formation of both the active metabolite and the 2-oxo-clopidogrel intermediate metabolite. Clopidogrel active metabolite pharmacokinetics and antiplatelet effects, as measured by ex vivo platelet aggregation assays, differ according to CYP2C19 genotype. Genetic variants of other CYP450 enzymes may also affect the formation of clopidogrel's active metabolite.

The CYP2C19*1 allele corresponds to fully functional metabolism while the CYP2C19*2 and *3 alleles are nonfunctional. CYP2C19*2 and *3 account for the majority of reduced function alleles in white (85%) and Asian (99%) poor metabolizers. Other alleles associated with absent or reduced metabolism are less frequent, and include, but are not limited to, CYP2C19*4, *5, *6, *7, and *8. A patient with poor metabolizer status will possess two loss-of-function alleles as defined above. Published frequencies for poor CYP2C19 metabolizer genotypes are approximately 2% for whites, 4% for blacks and 14% for Chinese. Tests are available to determine a patient's CYP2C19 genotype.

A crossover study in 40 healthy subjects, 10 each in the four CYP2C19 metabolizer groups, evaluated pharmacokinetic and antiplatelet responses using 300 mg followed by 75 mg per day and 600 mg followed by 150 mg per day, each for a total of 5 days. Decreased active metabolite exposure and diminished inhibition of platelet aggregation were observed in the poor metabolizers as compared to the other groups. When poor metabolizers received the 600 mg/150 mg regimen, active metabolite exposure and antiplatelet response were greater than with the 300 mg/75 mg regimen (see Table 3). An appropriate dose regimen for this patient population has not been established in clinical outcome trials.

Table 3: Active Metabolite Pharmacokinetics and Antiplatelet Responses by CYP2C19 Metabolizer Status
 | Dose | Ultrarapid (n=10) | Extensive (n=10) | Intermediate (n=10) | Poor (n=10)
Cmax (ng/mL) | 300 mg (24 h) | 24 (10) | 32 (21) | 23 (11) | 11 (4)
 | 600 mg (24 h) | 36 (13) | 44 (27) | 39 (23) | 17 (6)
 | 75 mg (Day 5) | 12 (6) | 13 (7) | 12 (5) | 4 (1)
 | 150 mg (Day 5) | 16 (9) | 19 (5) | 18 (7) | 7 (2)
IPA (%) [Inhibition of platelet aggregation with 5µM ADP; larger value indicates greater platelet inhibition] | 300 mg (24 h) | 40 (21) | 39 (28) | 37 (21) | 24 (26)
 | 600 mg (24 h) | 51 (28) | 49 (23) | 56 (22) | 32 (25)
 | 75 mg (Day 5) | 56 (13) | 58 (19) | 60 (18) | 37 (23)
 | 150 mg (Day 5) | 68 (18) | 73 (9) | 74 (14) | 61 (14)
VASP-PRI (%) [Vasodilator-stimulated phosphoprotein – platelet reactivity index; smaller value indicates greater platelet inhibition] | 300 mg (24 h) | 73 (12) | 68 (16) | 77 (12) | 91 (12)
 | 600 mg (24 h) | 51 (20) | 48 (20) | 56 (26) | 85 (14)
 | 75 mg (Day 5) | 40 (9) | 39 (14) | 50 (16) | 83 (13)
 | 150 mg (Day 5) | 20 (10) | 24 (10) | 29 (11) | 61 (18)
Values are mean (SD)

Some published studies suggest that intermediate metabolizers have decreased active metabolite exposure and diminished antiplatelet effects.

The relationship between CYP2C19 genotype and Plavix treatment outcome was evaluated in retrospective analyses of Plavix-treated subjects in CHARISMA (n=4862) and TRITON-TIMI 38 (n=1477), and in several published cohort studies. In TRITON-TIMI 38 and the majority of the cohort studies, the combined group of patients with either intermediate or poor metabolizer status had a higher rate of cardiovascular events (death, myocardial infarction, and stroke) or stent thrombosis compared to extensive metabolizers. In CHARISMA and one cohort study, the increased event rate was observed only in poor metabolizers.

13 NONCLINICAL TOXICOLOGY

13.1 Carcinogenesis, Mutagenesis, Impairment of Fertility

There was no evidence of tumorigenicity when clopidogrel was administered for 78 weeks to mice and 104 weeks to rats at dosages up to 77 mg/kg per day, which afforded plasma exposures >25 times that in humans at the recommended daily dose of 75 mg.

Clopidogrel was not genotoxic in four in vitro tests (Ames test, DNA-repair test in rat hepatocytes, gene mutation assay in Chinese hamster fibroblasts, and metaphase chromosome analysis of human lymphocytes) and in one in vivo test (micronucleus test by oral route in mice).

Clopidogrel was found to have no effect on fertility of male and female rats at oral doses up to 400 mg/kg per day (52 times the recommended human dose on a mg/m^2 basis).

14 CLINICAL STUDIES

The clinical evidence of the efficacy of Plavix is derived from three double-blind trials involving 77,599 patients. The CAPRIE study (Clopidogrel vs. Aspirin in Patients at Risk of Ischemic Events) was a comparison of Plavix to aspirin. The CURE (Clopidogrel in Unstable Angina to Prevent Recurrent Ischemic Events) and the COMMIT/CCS-2 (Clopidogrel and Metoprolol in Myocardial Infarction Trial / Second Chinese Cardiac Study) studies were comparisons of Plavix to placebo, given in combination with aspirin and other standard therapy. The CHARISMA (Clopidogrel for High Atherothrombotic Risk Ischemic Stabilization, Management, and Avoidance) study (n=15,603) also compared Plavix to placebo, given in combination with aspirin and other standard therapy.

14.1 Acute Coronary Syndrome

CURE

The CURE study included 12,562 patients with ACS without ST-elevation (UA or NSTEMI) and presenting within 24 hours of onset of the most recent episode of chest pain or symptoms consistent with ischemia. Patients were required to have either ECG changes compatible with new ischemia (without ST-elevation) or elevated cardiac enzymes or troponin I or T to at least twice the upper limit of normal. The patient population was largely Caucasian (82%) and included 38% women, and 52% patients ≥65 years of age.

Patients were randomized to receive Plavix (300-mg loading dose followed by 75 mg once daily) or placebo, and were treated for up to one year. Patients also received aspirin (75–325 mg once daily) and other standard therapies such as heparin. The use of GPIIb/IIIa inhibitors was not permitted for three days prior to randomization.

The number of patients experiencing the primary outcome (CV death, MI, or stroke) was 582 (9.3%) in the Plavix-treated group and 719 (11.4%) in the placebo-treated group, a 20% relative risk reduction (95% CI of 10%–28%; p < 0.001) for the Plavix-treated group (see Table 4).

Table 4: Outcome Events in the CURE Primary Analysis
Outcome | Plavix (+ aspirin) [Other standard therapies were used as appropriate.] | Placebo (+ aspirin) | Relative Risk Reduction (%) (95% CI)
 | (n=6259) | (n=6303)
Primary outcome (Cardiovascular death, MI, stroke) | 582 (9.3%) | 719 (11.4%) | 20% (10.3, 27.9) p < 0.001
All Individual Outcome Events: [The individual components do not represent a breakdown of the primary and co-primary outcomes, but rather the total number of subjects experiencing an event during the course of the study.]
CV death | 318 (5.1%) | 345 (5.5%) | 7% (-7.7, 20.6)
MI | 324 (5.2%) | 419 (6.6%) | 23% (11.0, 33.4)
Stroke | 75 (1.2%) | 87 (1.4%) | 14% (-17.7, 36.6)

Most of the benefit of Plavix occurred in the first two months, but the difference from placebo was maintained throughout the course of the trial (up to 12 months) (see Figure 1).

BOXED WARNING

Figure 1: Cardiovascular Death, Myocardial Infarction, and Stroke in the CURE Study

In CURE, the use of Plavix was associated with a lower incidence of CV death, MI or stroke in patient populations with different characteristics, as shown in Figure 2. The benefits associated with Plavix were independent of the use of other acute and long-term cardiovascular therapies, including heparin/LMWH, intravenous glycoprotein IIb/IIIa (GPIIb/IIIa) inhibitors, lipid-lowering drugs, beta-blockers, and ACE-inhibitors. The efficacy of Plavix was observed independently of the dose of aspirin (75–325 mg once daily). The use of oral anticoagulants, non-study anti-platelet drugs, and chronic NSAIDs was not allowed in CURE.

BOXED WARNING

Figure 2: Hazard Ratio for Patient Baseline Characteristics and On-Study Concomitant Medications/Interventions for the CURE Study

The use of Plavix in CURE was associated with a decrease in the use of thrombolytic therapy (71 patients [1.1%] in the Plavix group, 126 patients [2.0%] in the placebo group; relative risk reduction of 43%), and GPIIb/IIIa inhibitors (369 patients [5.9%] in the Plavix group, 454 patients [7.2%] in the placebo group, relative risk reduction of 18%). The use of Plavix in CURE did not affect the number of patients treated with CABG or PCI (with or without stenting), (2253 patients [36.0%] in the Plavix group, 2324 patients [36.9%] in the placebo group; relative risk reduction of 4.0%).

COMMIT

In patients with STEMI, the safety and efficacy of Plavix were evaluated in the randomized, placebo-controlled, double-blind study, COMMIT. COMMIT included 45,852 patients presenting within 24 hours of the onset of the symptoms of myocardial infarction with supporting ECG abnormalities (i.e., ST-elevation, ST-depression or left bundle-branch block). Patients were randomized to receive Plavix (75 mg once daily) or placebo, in combination with aspirin (162 mg per day), for 28 days or until hospital discharge, whichever came first.

The primary endpoints were death from any cause and the first occurrence of re-infarction, stroke or death.

The patient population included 28% women, 58% age ≥ 60 years (26% age ≥ 70 years), 55% patients who received thrombolytics, 68% who received ACE-inhibitors, and only 3% who underwent PCI.

As shown in Table 5 and Figures 3 and 4 below, Plavix significantly reduced the relative risk of death from any cause by 7% (p=0.029), and the relative risk of the combination of re-infarction, stroke or death by 9% (p=0.002).

Table 5: Outcome Events in the COMMIT Analysis
Event | Plavix (+ aspirin) (N=22961) | Placebo (+ aspirin) (N=22891) | Odds ratio (95% CI) | p-value
Composite endpoint: Death, MI, or Stroke [The difference between the composite endpoint and the sum of death+non-fatal MI+non-fatal stroke indicates that 9 patients (2 clopidogrel and 7 placebo) suffered both a non-fatal stroke and a non-fatal MI.] | 2121 (9.2%) | 2310 (10.1%) | 0.91 (0.86, 0.97) | 0.002
Death | 1726 (7.5%) | 1845 (8.1%) | 0.93 (0.87, 0.99) | 0.029
Non-fatal MI [Non-fatal MI and non-fatal stroke exclude patients who died (of any cause).] | 270 (1.2%) | 330 (1.4%) | 0.81 (0.69, 0.95) | 0.011
Non-fatal Stroke | 127 (0.6%) | 142 (0.6%) | 0.89 (0.70, 1.13) | 0.33

BOXED WARNING

Figure 3: Cumulative Event Rates for Death in the COMMIT Study [All treated patients received aspirin.]

BOXED WARNING

Figure 4: Cumulative Event Rates for the Combined End point Re-Infarction, Stroke or Death in the COMMIT Study [All treated patients received aspirin.]

The effect of Plavix did not differ significantly in various pre-specified subgroups as shown in Figure 5. The effect was also similar in non-prespecified subgroups including those based on infarct location, Killip class or prior MI history (see Figure 6). Such subgroup analyses should be interpreted cautiously.

BOXED WARNING

Figure 5: Effects of Adding Plavix to Aspirin on the Combined Primary Endpoint across Baseline and Concomitant Medication Subgroups for the COMMIT Study

* Three similar-sized prognostic index groups were based on absolute risk of primary composite outcome for each patient calculated from baseline prognostic variables (excluding allocated treatments) with a Cox regression model.

BOXED WARNING

Figure 6: Effects of Adding Plavix to Aspirin in the Non-Prespecified Subgroups in the COMMIT Study

14.2 Recent Myocardial Infarction, Recent Stroke, or Established Peripheral Arterial Disease

CAPRIE

The CAPRIE trial was a 19,185-patient, 304-center, international, randomized, double-blind, parallel-group study comparing Plavix (75 mg daily) to aspirin (325 mg daily). The patients randomized had: 1) recent histories of myocardial infarction (within 35 days); 2) recent histories of ischemic stroke (within 6 months) with at least a week of residual neurological signs; or 3) established peripheral arterial disease. Patients received randomized treatment for an average of 1.6 years (maximum of 3 years).

The trial's primary outcome was the time to first occurrence of new ischemic stroke (fatal or not), new myocardial infarction (fatal or not), or other vascular death. Deaths not easily attributable to nonvascular causes were all classified as vascular.

Table 6: Outcome Events in the CAPRIE Primary Analysis
 | Plavix | aspirin
Patients | n=9599 | n=9586
Ischemic stroke (fatal or not) | 438 (4.6%) | 461 (4.8%)
MI (fatal or not) | 275 (2.9%) | 333 (3.5%)
Other vascular death | 226 (2.4%) | 226 (2.4%)
Total | 939 (9.8%) | 1020 (10.6%)

As shown in the table, Plavix was associated with a lower incidence of outcome events, primarily MI. The overall relative risk reduction (9.8% vs. 10.6%) was 8.7%, p=0.045. Similar results were obtained when all-cause mortality and all-cause strokes were counted instead of vascular mortality and ischemic strokes (risk reduction 6.9%). In patients who survived an on-study stroke or myocardial infarction, the incidence of subsequent events was lower in the Plavix group.

The curves showing the overall event rate are shown in Figure 7. The event curves separated early and continued to diverge over the 3-year follow-up period.

BOXED WARNING

Figure 7: Fatal or Non-Fatal Vascular Events in the CAPRIE Study

The statistical significance favoring Plavix over aspirin was marginal (p=0.045). However, because aspirin is itself effective in reducing cardiovascular events in patients with recent myocardial infarction or stroke, the effect of Plavix is substantial.

The CAPRIE trial included a population that was randomized on the basis of 3 entry criteria. The efficacy of Plavix relative to aspirin was heterogeneous across these randomized subgroups (p=0.043). It is not clear whether this difference is real or a chance occurrence. Although the CAPRIE trial was not designed to evaluate the relative benefit of Plavix over aspirin in the individual patient subgroups, the benefit appeared to be strongest in patients who were enrolled because of peripheral vascular disease (especially those who also had a history of myocardial infarction) and weaker in stroke patients. In patients who were enrolled in the trial on the sole basis of a recent myocardial infarction, Plavix was not numerically superior to aspirin.

14.3 Lack of Established Benefit of Plavix plus Aspirin in Patients with Multiple Risk Factors or Established Vascular Disease

CHARISMA

The CHARISMA trial was a 15,603 subject, randomized, double-blind, parallel group study comparing Plavix (75 mg daily) to placebo for prevention of ischemic events in patients with vascular disease or multiple risk factors for atherosclerosis. All subjects were treated with aspirin 75–162 mg daily. The mean duration of treatment was 23 months. The study failed to demonstrate a reduction in the occurrence of the primary endpoint, a composite of CV death, MI, or stroke. A total of 534 (6.9%) patients in the Plavix group versus 573 (7.4%) patients in the placebo group experienced a primary outcome event (p=0.22). Bleeding of all severities was more common in the subjects randomized to Plavix.

16 HOW SUPPLIED/STORAGE AND HANDLING

Plavix (clopidogrel bisulfate) 75 mg tablets are available as pink, round, biconvex, film-coated tablets debossed with "75" on one side and "1171" on the other. Tablets are provided as follows:

NDC 21695-665-30 Bottles of 30
NDC 21695-665-90 Bottles of 90

STORAGE AND HANDLING

Store at 25° C (77° F); excursions permitted to 15°–30° C (59°–86° F) [see USP Controlled Room Temperature].

17 PATIENT COUNSELING INFORMATION

17.1 Benefits and Risks

- Summarize the effectiveness features and potential side effects of Plavix.
- Tell patients to take Plavix exactly as prescribed.
- Remind patients not to discontinue Plavix without first discussing it with the physician who prescribed Plavix.

17.2 Bleeding

Inform patients that they:

- will bruise and bleed more easily.
- will take longer than usual to stop bleeding.
- should report any unanticipated, prolonged, or excessive bleeding, or blood in their stool or urine.

17.3 Other Signs and Symptoms Requiring Medical Attention

- Inform patients that TTP is a rare but serious condition that has been reported with Plavix and other drugs in this class of drugs.
- Instruct patients to get prompt medical attention if they experience any of the following symptoms that cannot otherwise be explained: fever, weakness, extreme skin paleness, purple skin patches, yellowing of the skin or eyes, or neurological changes.

17.4 Invasive Procedures

Instruct patients to:

- inform physicians and dentists that they are taking Plavix before any invasive procedure is scheduled.
- tell the doctor performing the invasive procedure to talk to the prescribing health care professional before stopping Plavix.

17.5 Concomitant Medications

Ask patients to list all prescription medications, over-the-counter medications, or dietary supplements they are taking or plan to take, including prescription or over-the-counter omeprazole, so the physician knows about other treatments that may affect how Plavix works (e.g., warfarin and NSAIDs) [see Warnings and Precautions (5)].

Distributed by:
Bristol-Myers Squibb/Sanofi Pharmaceuticals Partnership
Bridgewater, NJ 08807

Plavix® is a registered trademark.

Repackaged by:

Rebel Distributors Cor

Thousand Oaks, CA 91320

PACKAGE LABEL

PRINCIPAL DISPLAY PANEL - 75 mg